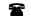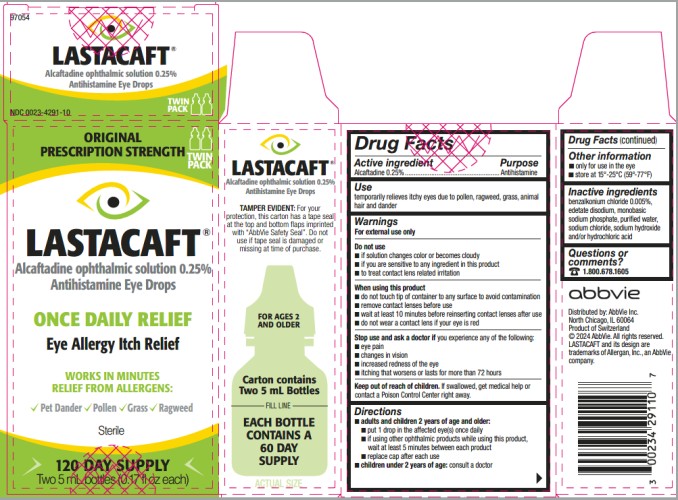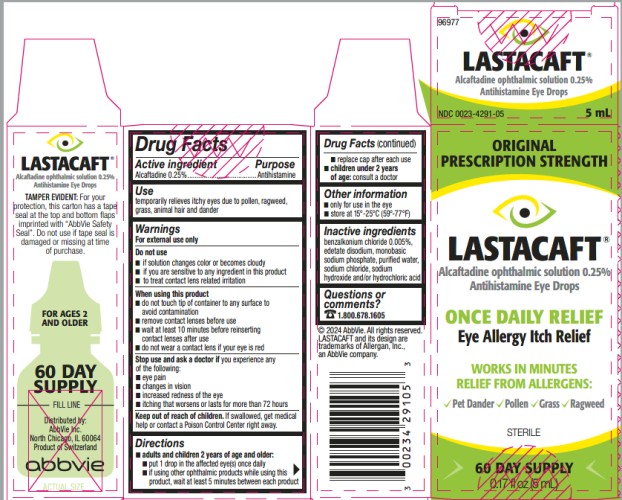 DRUG LABEL: LASTACAFT
NDC: 0023-4291 | Form: SOLUTION/ DROPS
Manufacturer: Allergan, Inc.
Category: otc | Type: HUMAN OTC DRUG LABEL
Date: 20220810

ACTIVE INGREDIENTS: alcaftadine 2.5 mg/1 mL
INACTIVE INGREDIENTS: BENZALKONIUM CHLORIDE; edetate disodium; sodium phosphate, monobasic; water; sodium chloride; sodium hydroxide; hydrochloric acid

LASTACAFT®
Antihistamine Eye Drops
Drug Facts

Active ingredient

Alcaftadine 0.25%

Purpose

Antihistamine

Use

temporarily relieves itchy eyes due to pollen, ragweed, grass, animal hair and dander

Warnings

For external use only

Do not use

■ if solution changes color or becomes cloudy

■ if you are sensitive to any ingredient in this product

■ to treat contact lens related irritation

When using this product

■ do not touch tip of container to any surface to avoid contamination

■ remove contact lenses before use

■ wait at least 10 minutes before reinserting contact lenses after use

■ do not wear a contact lens if your eye is red

Stop use and ask a doctor if

you experience any of the following:

■ eye pain

■ changes in vision

■ increased redness of the eye

■ itching that worsens or lasts for more than 72 hours

Keep out of reach of children.

If swallowed, get medical help or contact a Poison Control Center right away.

Directions

- adults and children 2 years of age and older:
  - put 1 drop in the affected eye(s) once daily
  - if using other ophthalmic products while using this product, wait at least 5 minutes between each product
  - replace cap after each use
- children under 2 years of age: consult a doctor

Other information

■ only for use in the eye

■ store at 15°-25°C (59°-77°F)

Inactive ingredients

benzalkonium chloride 0.005%, edetate disodium, monobasic sodium phosphate, purified water, sodium chloride, sodium hydroxide and/or hydrochloric acid

Questions or comments?

1.800.678.1605

PRINCIPAL DISPLAY PANEL

NDC 0023-4291-10
ORIGINAL
PRESCRIPTION STRENGTH
LASTACAFT®
Alcaftadine ophthalmic solution 0.25%
Antihistamine Eye Drops
ONCE DAILY RELIEF
Eye Allergy Itch Relief
WORKS IN MINUTES
RELIEF FROM ALLERGENS:
Pet Dander Pollen Grass Ragweed
STERILE
120 DAY SUPPLY
Two 5 mL bottles (0.17 fl oz each)

PRINCIPAL DISPLAY PANEL

NDC 0023-4291-05
ORIGINAL
PRESCRIPTION STRENGTH
LASTACAFT®
Alcaftadine ophthalmic solution 0.25%
Antihistamine Eye Drops
ONCE DAILY RELIEF
Eye Allergy Itch Relief
WORKS IN MINUTES
RELIEF FROM ALLERGENS:
Pet Dander Pollen Grass Ragweed
STERILE
60 DAY SUPPLY
0.17 fl oz (5 mL)